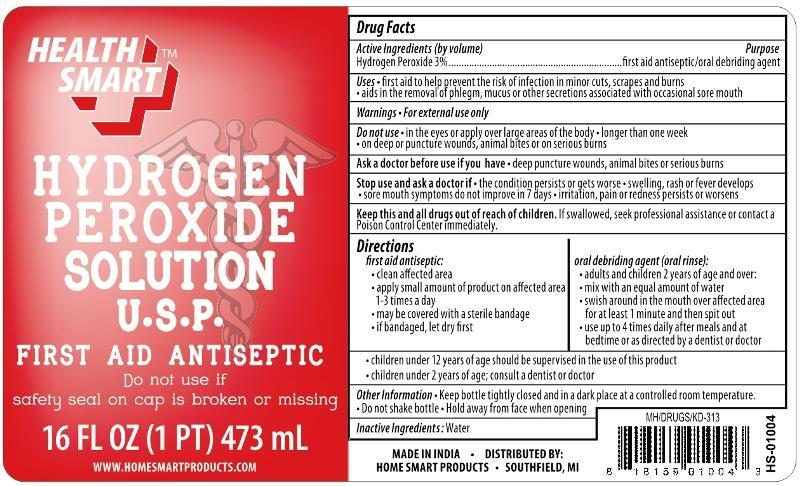 DRUG LABEL: Hydrogen Peroxide
NDC: 52862-007 | Form: LIQUID
Manufacturer: Home Smart Products
Category: otc | Type: HUMAN OTC DRUG LABEL
Date: 20181231

ACTIVE INGREDIENTS: HYDROGEN PEROXIDE 3 mL/100 mL
INACTIVE INGREDIENTS: WATER

HEALTH SMART HYDROGEN PEROXIDE

Active ingredient (by volume)

Hydrogen Peroxide 3%

Purpose

first aid antiseptic/oral debriding agent

Uses

- first aid to help prevent the risk of infection in minor cuts, scrapes and burns
- aids in the removal of phlegm, mucus or other secretions associated with occasional sore mouth

Warnings

For external use only

Do not use

- in the eyes or apply over large areas of the body
- longer than one week
- on deep or puncture wounds, animal bites or on serious burns

Ask a doctor before use if you have deep puncture wounds, animal bites or serious burns

Stop use and ask a doctor if

- the condition persists or gets worse
- swelling, rash or fever develops
- sore mouth symptoms do not improve in 7 days
- irritation, pain, or redness persists or worsens

KEEP OUT OF REACH OF CHILDREN

Keep this and all drugs out of reach of children.

If swallowed, seek professional assistance or contact a Poison Control Center immediately.

Directions

first aid antiseptic:

- clean the affected area
- apply small amount of product on the affected area 1-3 times a day
- may be covered with a sterile bandage
- if bandaged, let dry first

oral debriding agent:

- adults and children 2 years of age and over:
- mix with equal amount of water
- swish around in the mouth over the affected area for at least 1 minute and then spit out
- use up to 4 times daily after meals and at bedtime or as directed by a dentist or doctor

- children under 12 years of age should be supervised in the use of this product
- children under 2 years of age: consult a dentist or doctor

Other information

- Keep bottle tightly closed and in a dark place at a controlled room temperature.
- Do not shake bottle.
- Hold away from face when opening.

Inactive ingredients

Water

PRINCIPAL DISPLAY PANEL

HEALTH SMART HYDROGEN PEROXIDE LIQUID
FIRST AID ANTISEPTIC/ORAL DEBRIDING AGENT

16 FL.OZ (473 mL)